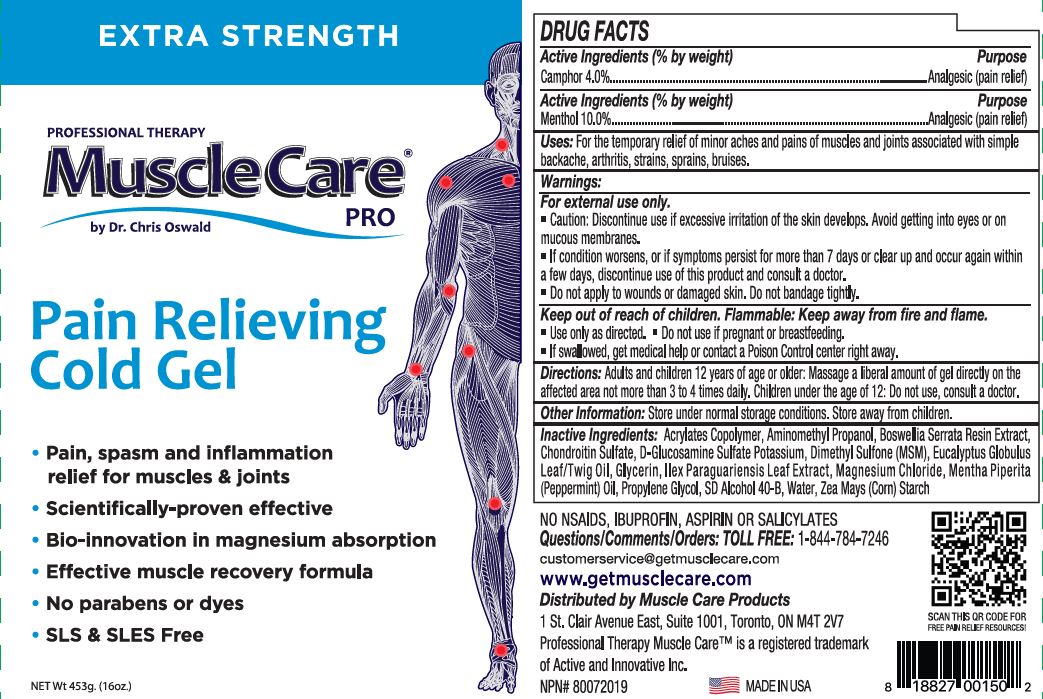 DRUG LABEL: Professional Therapy MuscleCare Pro
NDC: 70039-302 | Form: GEL
Manufacturer: ACTIVE AND INNOVATIVE, LLC
Category: otc | Type: HUMAN OTC DRUG LABEL
Date: 20240503

ACTIVE INGREDIENTS: CAMPHOR (SYNTHETIC) 4 g/100 g; MENTHOL 10 g/100 g
INACTIVE INGREDIENTS: ACRYLATES/C10-30 ALKYL ACRYLATE CROSSPOLYMER (60000 MPA.S); AMINOMETHYLPROPANOL; INDIAN FRANKINCENSE; CHONDROITIN SULFATE (BOVINE); GLUCOSAMINE SULFATE POTASSIUM CHLORIDE; DIMETHYL SULFONE; EUCALYPTUS OIL; GLYCERIN; ILEX PARAGUARIENSIS LEAF; MAGNESIUM CHLORIDE; PEPPERMINT OIL; PROPYLENE GLYCOL; ALCOHOL; WATER; STARCH, CORN

ACTIVE AND INNOVATIVE (as PLD) - MUSCLECARE COLD GEL (70039-302)

Active Ingredietns (% by weight)

Camphor 4%

Menthol 10%

Purpose

Analgesic Pain Relief

Uses:

For the temporary relief of minor aches and pains of muscles and joints associated with simple backache, arthritis, strains, sprains, bruises.

Warnings:

For external use only.

- Catution: Discontinue use if excessive irritation of the skin develops. Avoid getting into eyes or on mucous membranes.
- If condition worsens, or if symptoms persist for more than 7 days or clear up and occur again within a few days, discontinue use of this product and consult a doctor.
- Do not apply to wounds or damaged skin. Do not bandage tighlty.

Keep out of reach of children. Flammable: Keep away from fire and flame.

- Use only as directed
- Do not use if pregnant or breastfeeding
- If swallowed, get medical help or contact a Poison Control center right away.

Directions

Adults and children 12 years of age or older: Massage a liberal amount of gel directly on the affected area not more than 3 to 4 times daily. Children under the age of 12: Do not use, consult a doctor.

Other Information

Store under normal storage conditions. Store away from children.

Inactive Ingredients

Acrylates Copolymer, Aminomethyl Propanol, Boswellia Serrata Resin Extract, Chondroitin Sulfate, D-Glucosamine Sulfate Potassium, Dimethyl Sulfone (MSM), Eucalyptus Globulus Leaf/Twig Oil, Glycerin, Ilex Paraguariensis Leaf Extract, Magnesium Chloride, Mentha Piperita (Peppermint) Oil, Propylene Glycol, SD Alcohol 40-B, Water, Zea Mays (Corn) Starch